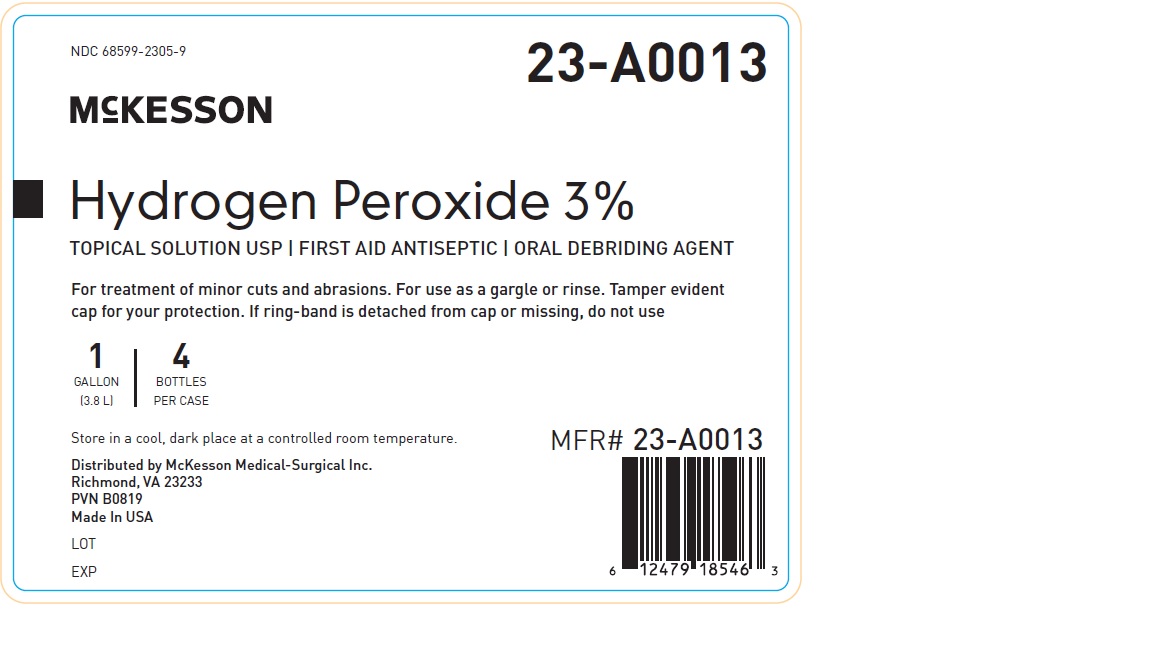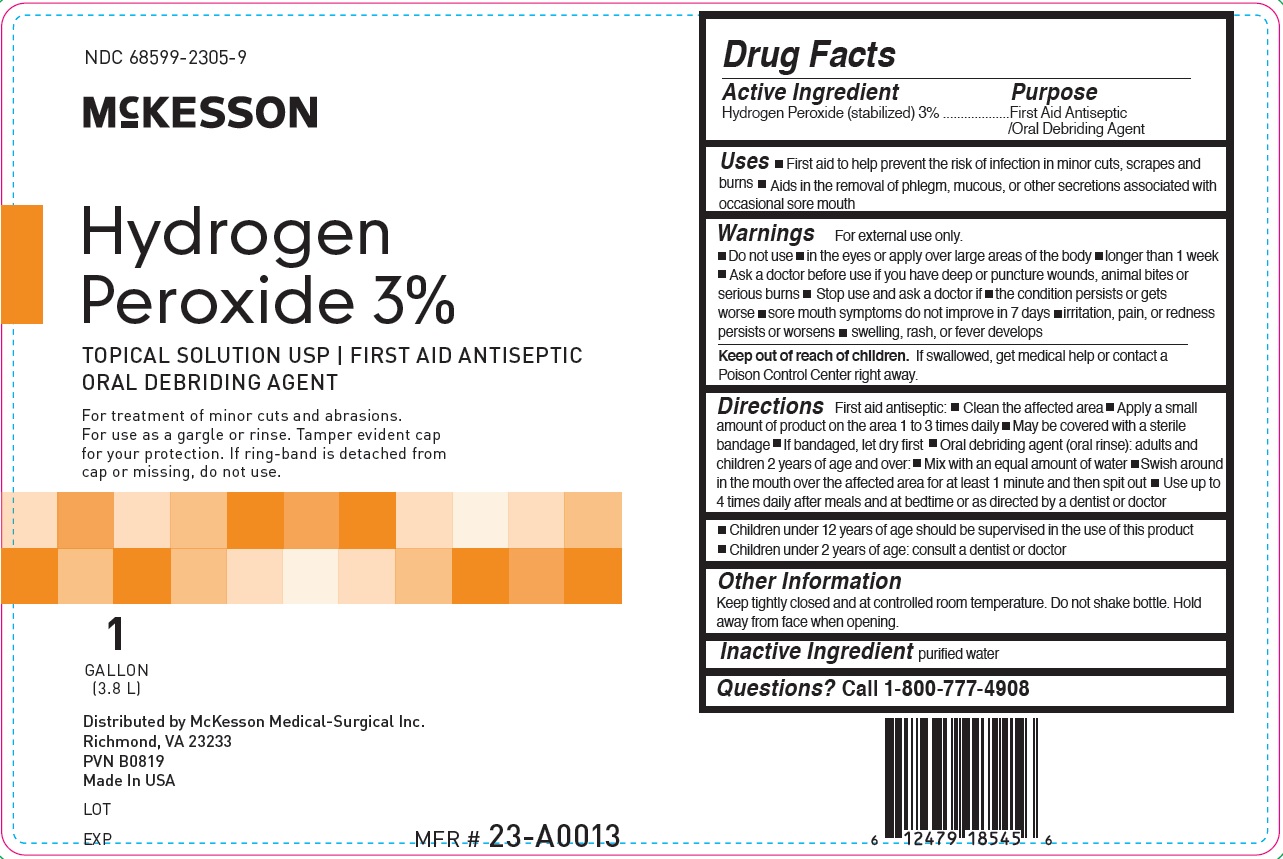 DRUG LABEL: Hydrogen Peroxide
NDC: 68599-2305 | Form: SOLUTION
Manufacturer: McKesson Medical-Surgical Inc.
Category: otc | Type: HUMAN OTC DRUG LABEL
Date: 20241115

ACTIVE INGREDIENTS: HYDROGEN PEROXIDE 30 mg/1 mL
INACTIVE INGREDIENTS: WATER

Hydrogen Peroxide

Drug Facts

Active Ingredient

Hydrogen Peroxide (stabilized) 3%

Purpose

First Aid Antiseptic/Oral Debriding Agent

Uses

- First aid to help prevent the risk of infection in minor cuts, scrapes and burns
- Aids in the removal of phlegm, mucous, or other secretions associated with occasional sore mouth

Warnings

- For external use only

- Do not use
  - in the eyes or apply over large areas of the body
  - longer than 1 week

- Ask a doctor before use if you have deep or puncture wounds, animal bites or serious burns

- Stop use and ask a doctor if
  - the condition persists or gets worse
  - sore mouth symptoms do not improve in 7 days
  - irritation, pain, or redness persists or worsens
  - swelling, rash, or fever develops

- Keep out of reach of children.If swallowed, get medical help or contact a Poison Control Center right away.

Directions

First aid antiseptic:

- Clean the affected area
- Apply a small amount of product on the area 1 to 3 times daily
- May be covered with a sterile bandage
- If bandaged, let dry first

Oral debriding agent (oral rinse):
adults and children 2 years of age and over:

- Mix with an equal amount of water
- Swish around in the mouth over the affected area for at least 1 minute and then spit out
- Use up to 4 times daily after meals and at bedtime or as directed by a dentist or doctor

- Children under 12 years of age should be supervised in the use of this product
- Children under 2 years of age: consult a dentist or doctor

Other Information

Keep tightly closed and at controlled room temperature. Do not shake bottle. Hold away from face when opening.

Inactive Ingredient

purified water

Distributed By McKesson Medical-Surgical Inc.
Richmond, VA 23228

PRINCIPAL DISPLAY PANEL - 3.8 L Bottle Label

NDC 68599-2305-9

McKESSON

Hydrogen
Peroxide 3%

TOPICAL SOLUTION USP
FIRST AID ANTISEPTIC
ORAL DEBRIDING AGENT

For treatment of minor cuts and abrasions.
For use as a gargle or rinse.

1
GALLON
(3.8 L)

TAMPER EVIDENT CAP FOR YOUR PROTECTION.

IF RING-BANDIS DETACHED FROM CAP OR MISSING DO NOT USE.

Distributed By McKesson Medical-Surgical Inc.
Richmond, VA 23233
VPN B0819
Made in USA

MFR # 23-A0013

Case